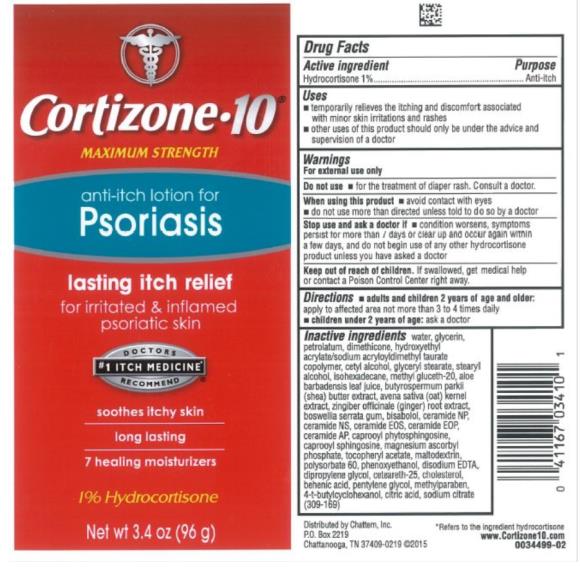 DRUG LABEL: Cortizone 10 for Psoriasis
NDC: 41167-0341 | Form: LOTION
Manufacturer: Chattem, Inc.
Category: otc | Type: HUMAN OTC DRUG LABEL
Date: 20231030

ACTIVE INGREDIENTS: HYDROCORTISONE 1 g/100 g
INACTIVE INGREDIENTS: WATER; GLYCERIN; PETROLATUM; DIMETHICONE; HYDROXYETHYL ACRYLATE/SODIUM ACRYLOYLDIMETHYL TAURATE COPOLYMER (45000 MPA.S AT 1%); CETYL ALCOHOL; GLYCERYL MONOSTEARATE; STEARYL ALCOHOL; ISOHEXADECANE; METHYL GLUCETH-20; ALOE VERA LEAF; SHEA BUTTER; OAT; GINGER; INDIAN FRANKINCENSE; BISABOLOL OXIDE B, (-)-; CERAMIDE 3; CERAMIDE 2; CERAMIDE EOS; CERAMIDE 1; CERAMIDE 6 II; N-HEXANOYLSPHINGOSINE; MAGNESIUM ASCORBYL PHOSPHATE; ALPHA-TOCOPHEROL ACETATE; MALTODEXTRIN; POLYSORBATE 60; PHENOXYETHANOL; EDETATE DISODIUM; DIPROPYLENE GLYCOL; CETEARETH-25; CHOLESTEROL; BEHENIC ACID; PENTYLENE GLYCOL; METHYLPARABEN; 4-TERT-BUTYLCYCLOHEXANOL; CITRIC ACID MONOHYDRATE; SODIUM CITRATE

Cortizone 10 for Psoriasis

Cortizone · 10®
Anti-Itch Lotion for Psoriasis

Drug Facts

Active Ingredient

Hydrocortisone 1%

Purpose

Anti-itch

Uses

- temporarily relieves the itching and discomfort associated with minor skin irritations and rashes
- other uses of this product should only be used under the advice and supervision of a doctor

Warnings

For external use only

Do not use

- for the treatment of diaper rash. Consult a doctor.

When using this product

- avoid contact with eyes
- do not use more than directed unless told to do so by a doctor

Stop use and ask a doctor if

- condition worsens, symptoms persist for more than 7 days or clear up and occur again within a few days, and do not begin use of any other hydrocortisone product unless you have asked a doctor

Keep out of reach of children.

- if swallowed, get medical help or contact a Poison Control Center right away.

Directions

- adults and children 2 years of age and older: apply to affected area not more than 3 to 4 times daily
- children under 2 years of age: ask a doctor

Inactive ingredients

water, glycerin, petrolatum, dimethicone, hydroxyethyl acrylate/sodium acryloyldimethyl taurate copolymer, cetyl alcohol, glyceryl stearate, stearyl alcohol, isohexadecane, methyl gluceth-20, aloe barbadensis leaf juice, butyrospermum parkii (shea) butter extract, avena sativa (oat) kernel extract, zingiber officinale (ginger) root extract, boswellia serrata gum, bisabolol, ceramide NP, ceramide NS, ceramide EOS, ceramide EOP, ceramide AP, caprooyl phytosphingosine, caprooyl sphingosine, magnesium ascorbyl phosphate, tocopheryl acetate, maltodextrin, polysorbate 60, phenoxyethanol, disodium EDTA, dipropylene glycol, ceteareth-25, cholesterol, behenic acid, pentylene glycol, methylparaben, 4-t-butylcyclohexanol, citric acid, sodium citrate

PRINCIPAL DISPLAY PANEL

Cortizone 10®
MAXIMUM STRENGTH
anti-itch lotion for
Psoriasis
1% Hydrocortisone
net wt 3.4 oz (96 g)